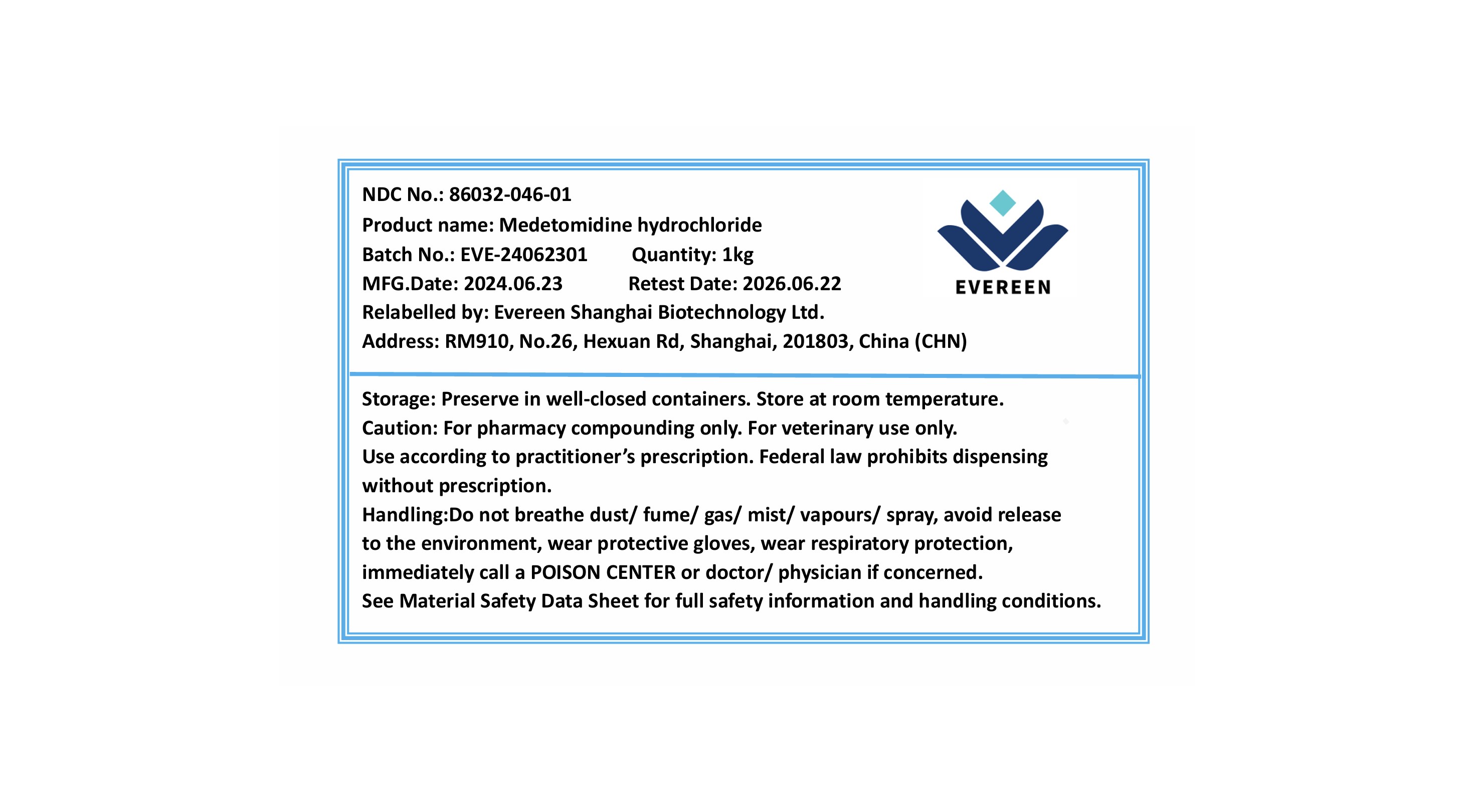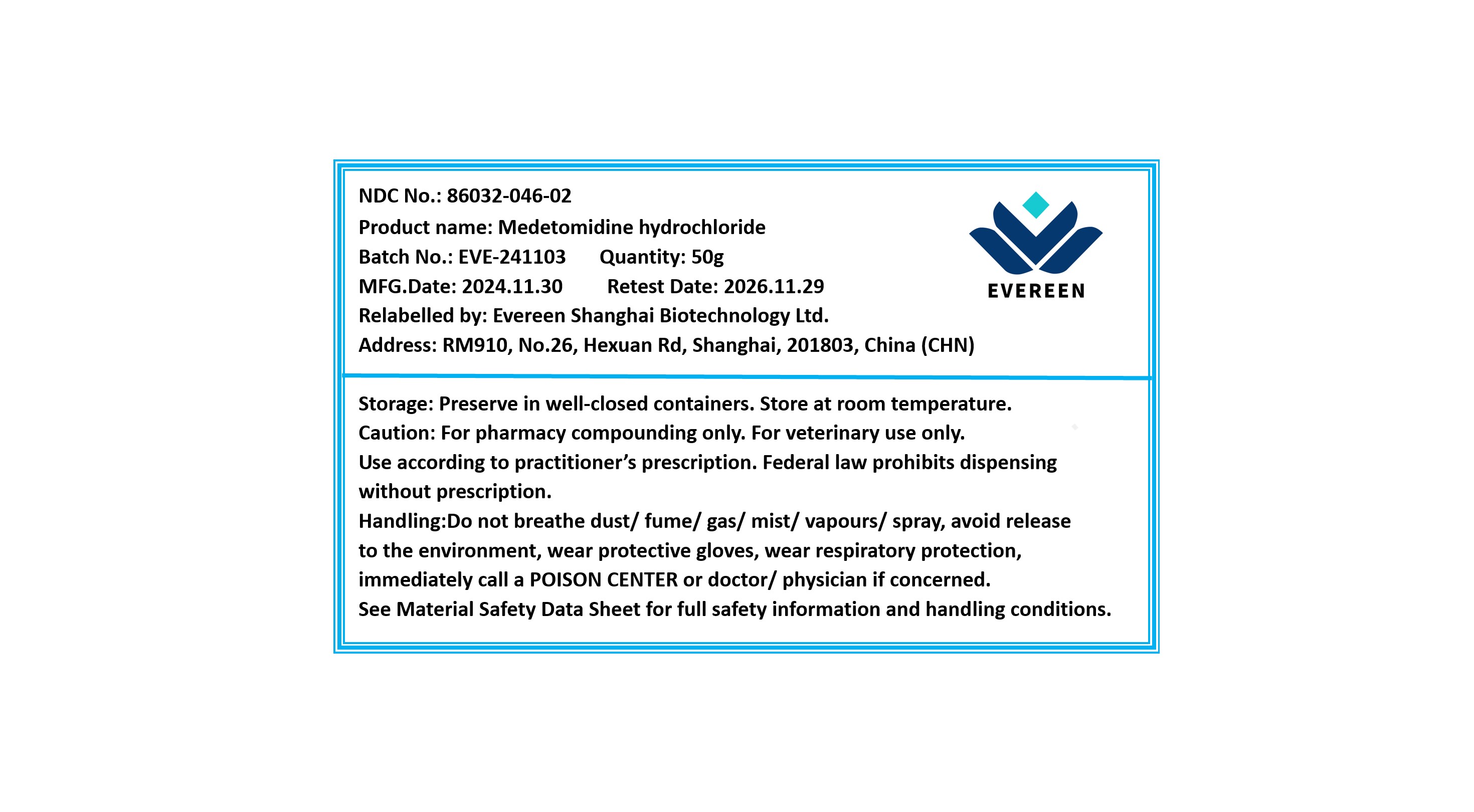 DRUG LABEL: Medetomidine hydrochloride
NDC: 86032-046 | Form: POWDER
Manufacturer: Evereen Shanghai Biotechnology Ltd.
Category: other | Type: BULK INGREDIENT - ANIMAL DRUG
Date: 20250916

ACTIVE INGREDIENTS: MEDETOMIDINE HYDROCHLORIDE 1 g/1 g

Medetomidine hydrochloride